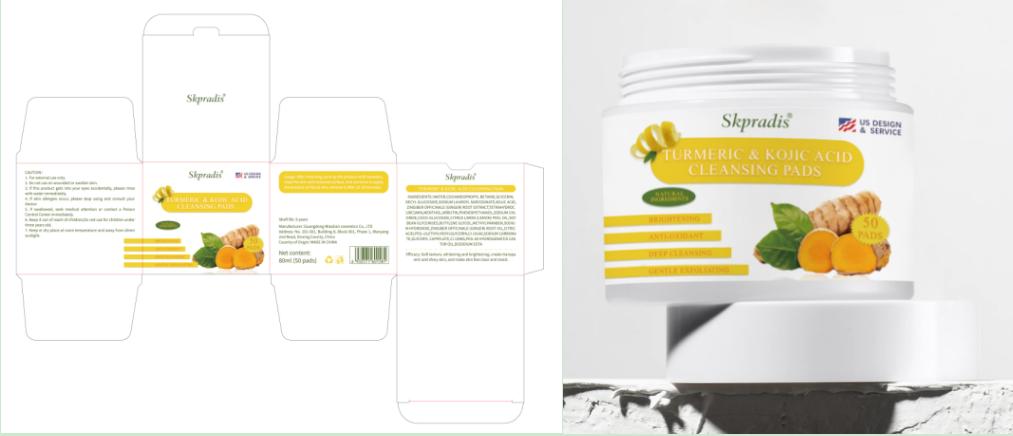 DRUG LABEL: Skpradis TURMERIC KOJIC ACID CLEANSING PADS
NDC: 84507-034 | Form: LIQUID
Manufacturer: Guangdong Miaolian Cosmetics Co., Ltd.
Category: otc | Type: HUMAN OTC DRUG LABEL
Date: 20250319

ACTIVE INGREDIENTS: KOJIC ACID 0.7 mg/100 mL
INACTIVE INGREDIENTS: ARBUTIN; ETHYLHEXYLGLYCERIN; CI 15985; EDETATE DISODIUM; COCAMIDOPROPYL BETAINE; GLYCERYL CAPRYLATE; CITRIC ACID; PHENOXYETHANOL; PEG-10; ZINGIBER OFFICINALE (GINGER) ROOT OIL; BUTYLENE GLYCOL; SODIUM HYDROXIDE; SODIUM CARBONATE; TETRAHYDROCURCUMIN DIACETATE; COCO-GLUCOSIDE; DECYL GLUCOSIDE; CI 19140; PEG-40 HYDROGENATED CASTOR OIL; SOYBEAN LECITHIN; SODIUM LAUROYL SARCOSINATE; METHYLPARABEN; CITRUS LIMON (LEMON) PEEL OIL; MENTHOL; GLYCERIN; SODIUM CHLORIDE; WATER

ACTIVE INGREDIENT

KOJIC ACID----0.7%

INDICATIONS AND USAGE

After cleansing, pick up the product with tweezers, wipe the skin with textured surface, and continue to apply the product on facial skin, remove it after 15-20 minutes.

INACTIVE INGREDIENT

WATER
COCAMIDOPROPYL BETAINE
GLYCERIN
DECYL GLUCOSIDE
SODIUM LAUROYL SARCOSINATE

TETRAHYDROCURCUMIN DIACETATE

MENTHOL
ARBUTIN
PHENOXYETHANOL
SODIUM CHLORIDE
COCO-GLUCOSIDE

CITRUS LIMON (LEMON) PEEL OIL

SOYBEAN

GLYCERIN

BUTYLENE GLYCOL
METHYLPARABEN
SODIUM HYDROXIDE
ZINGIBER OFFICINALE (GINGER) ROOT OIL
CITRIC ACID
PEG-10
ETHYLHEXYLGLYCERIN
CI 19140
SODIUM CARBONATE
GLYCERYL CAPRYLATE
CI 15985
PEG-40 HYDROGENATED CASTOR OIL

EDETATE DISODIUM

DOSAGE AND ADMINISTRATION

Soft texture, whitening and brightening, create transparent and shiny skin, and make skin feel clear and moist.

KEEP OUT OF REACH OF CHILDREN

Please keep out of reach of children. Do not swallow

PURPOSE

1. Adding turmeric and kojic acid can reduce the onset of acne, lighten dark spots,promote even skin tone, and make the skin more radiant.
2. Deeply clean the skin, remove dirt and excess oil, and prevent pores from being clogged.
3. It can deeply nourish the skin, long-lasting moisturizing, restore the skin's moisture and fullness, andrejuvenate it.

WARNINGS

Please keep out of reach of children.Do not swallow.Please clean your hands before use to ensure the best results from the product.Discontinue use if signs of irritation or rash occur.Store in a cool and dry place.